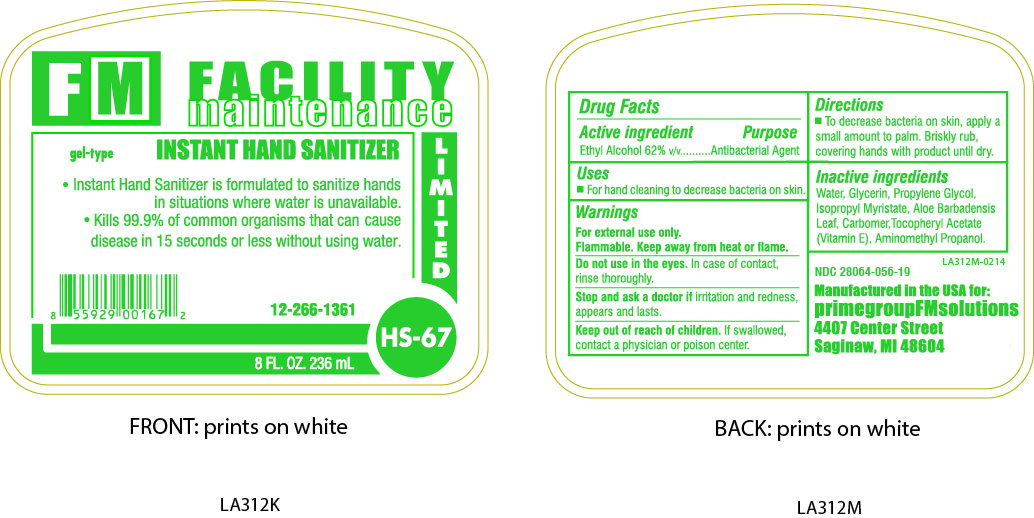 DRUG LABEL: Instant Hand Sanitizer
NDC: 28064-056 | Form: SOLUTION
Manufacturer: Knight Facilities Management, Inc.
Category: otc | Type: HUMAN OTC DRUG LABEL
Date: 20140227

ACTIVE INGREDIENTS: ALCOHOL 62 mL/100 mL
INACTIVE INGREDIENTS: WATER; POLYACRYLIC ACID (250000 MW); GLYCERIN; PROPYLENE GLYCOL; ISOPROPYL MYRISTATE; AMINOMETHYLPROPANOL; ALOE VERA LEAF; ALPHA-TOCOPHEROL ACETATE

Instant Hand Sanitizer

ACTIVE INGREDIENT

Ethyl Alcohol 62% v/v.....Antibacterial Agent

INACTIVE INGREDIENT

Water, Glycerin, Propylene Glycol, Isopropyl Myristate, Aloe Barbadensis Leaf, Carbomer, Tocopheryl Acetate (Vitamin E), Aminomethyl Propanol

PURPOSE

For hand cleaning to decrease bacteria on skin.

WARNINGS

For external use only.

Flammable. Keep away from heat or flame.

Do not use in the eyes. In case of contact, rinse thoroughly.

Stop use and ask doctor if irritation and redness, appears and lasts.

Keep out of reach of children. If swallowed, contact a physician or poison center.

DOSAGE AND ADMINISTRATION

To decrease bacteria on skin, apply a small amount to palm. Briskly rub, covering hands with product until dry.

INDICATIONS AND USAGE

For hand cleaning to decrease bacteria on skin.

Do not use in the eyes. In case of contact, rinse thoroughly.

Stop use and ask doctor if irritation and redness, appears and lasts.

Keep out of reach of children. If swallowed, contact a physician or poison center.

Keep out of reach of children. If swallowed, contact a physician or poison center.

PACKAGE LABEL

28064-056-19.jpg